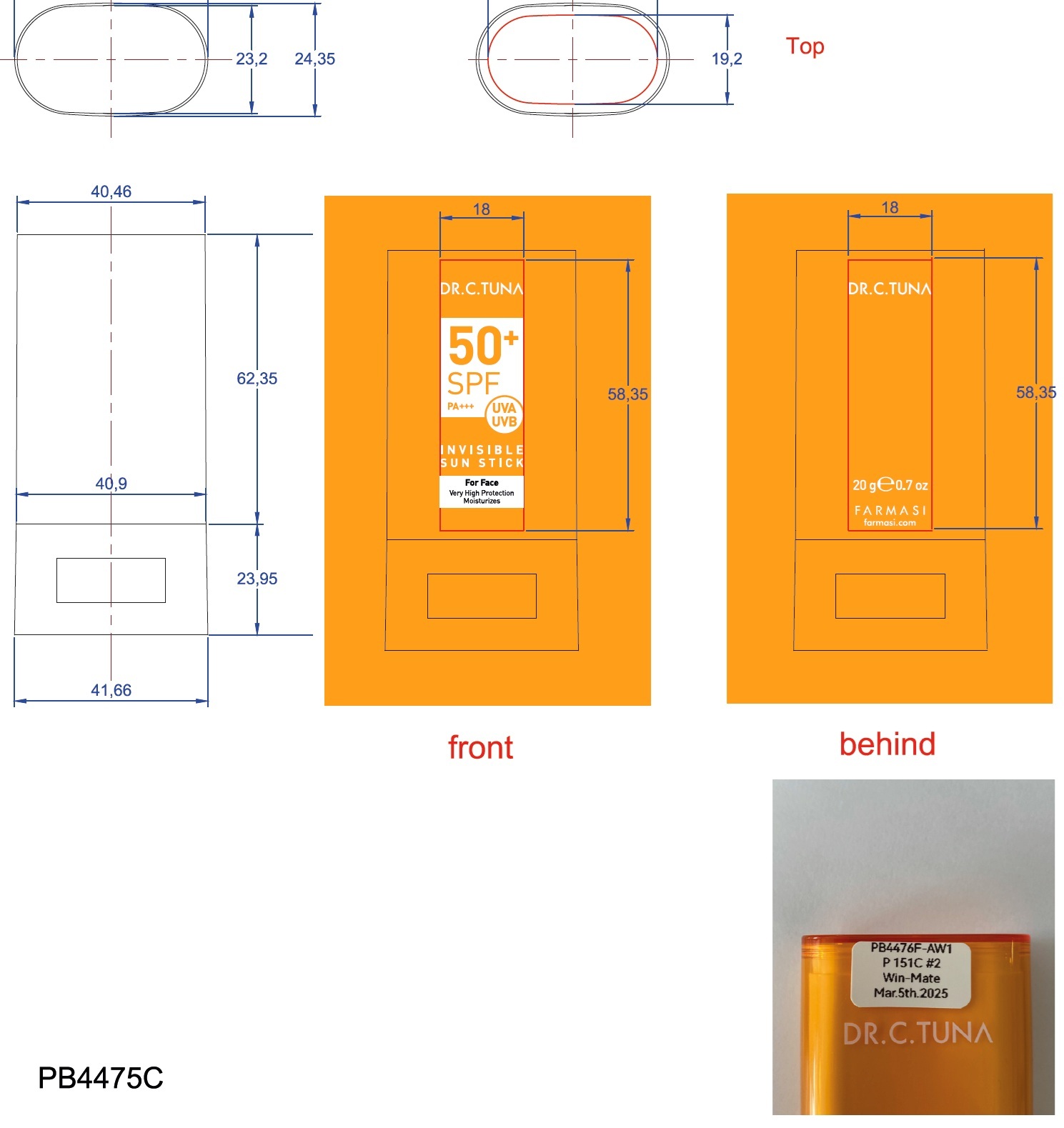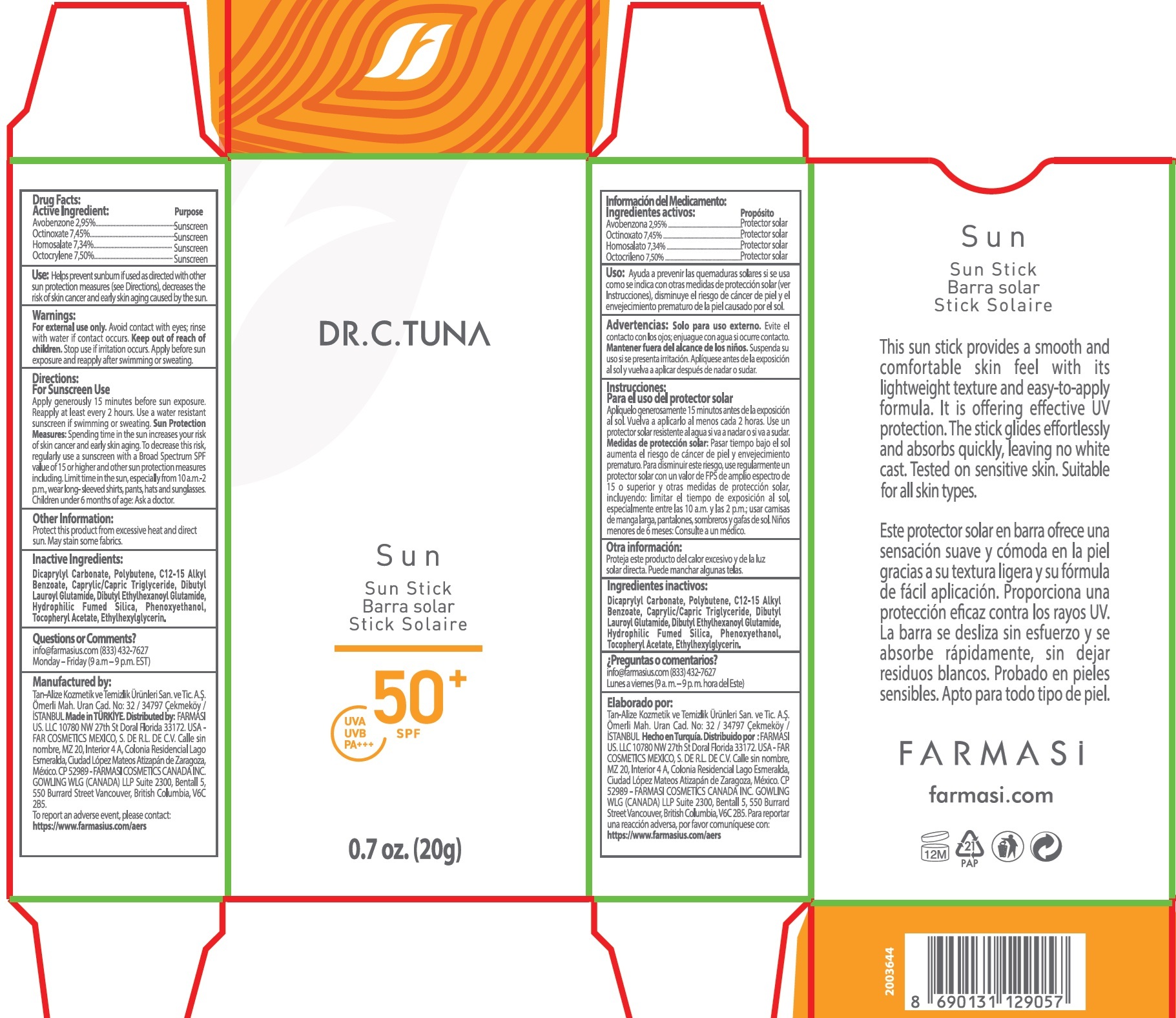 DRUG LABEL: Dr. C. Tuna Sun Stick SPF 50
NDC: 74690-028 | Form: STICK
Manufacturer: Farmasi US LLC
Category: otc | Type: HUMAN OTC DRUG LABEL
Date: 20260202

ACTIVE INGREDIENTS: AVOBENZONE 29.5 mg/1 g; OCTINOXATE 74.5 mg/1 g; HOMOSALATE 73.4 mg/1 g; OCTOCRYLENE 75 mg/1 g
INACTIVE INGREDIENTS: ALKYL (C12-15) BENZOATE; MEDIUM-CHAIN TRIGLYCERIDES; DIBUTYL LAUROYL GLUTAMIDE; DIBUTYL ETHYLHEXANOYL GLUTAMIDE; PHENOXYETHANOL; .ALPHA.-TOCOPHEROL ACETATE; ETHYLHEXYLGLYCERIN; DICAPRYLYL CARBONATE

Dr. C. Tuna Sun Stick SPF 50

Active Ingredient:

Avobenzone 2,95%,

Octinoxate 7,45%,

Homosalate 7,34%,

Octocrylene 7,50%

Purpose

Sunscreen

Use:

Helps preventsunburn if used as directed with other sun protection measures (see Directions), decreases the risk of skin cancer and early skin aging caused by the sun.

Warnings:

For external use only.Avoid contact with eyes; rinse with water if contact occurs.

Keep out of reach of children.

Stop use if irritation occurs. Apply before sun exposure and reapply after swimming or sweating.

Directions:

For Sunscreen Use

Apply generously 15 minutes before sun exposure. Reapply at least every 2 hours. Use a water resistant sunscreen if swimming or sweating. Sun Protection Measures:Spending time in the sun increases your risk of skin cancer and early skin aging. To decrease this risk, regularly use a sunscreen with a Broad Spectrum SPF value of 15 or higher and other sun protection measures including. Limit time in the sun, especiallyfrom 10 a.m.-2 prn„ wear long- sleeved shirts, pants, hats and sunglasses. Children under 6 months of age: Ask a doctor.

Other Information:

Protect this product from excessive heat and direct sun. May stain some fabrics.

Inactive Ingredients:

Dicaprylyl Carbonate, Polybutene, C12-15 Alkyl Benzoate, Caprylic/Capric Triglyceride, Dibutyl Lauroyl Glutamide, Dibutyl Ethylhexanoyl Glutamide, Hydrophilic Fumed Silica, Phenoxyethanol, Tocopheryl Acetate, Ethylhexylglycerin.

Questions or Comments?

inf0@farmasiuscom (833) 432-7627 Monday - Friday (9 a.m - 9 p.m. EST)